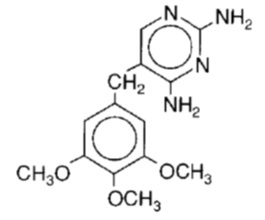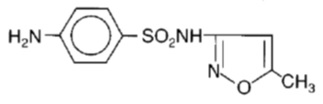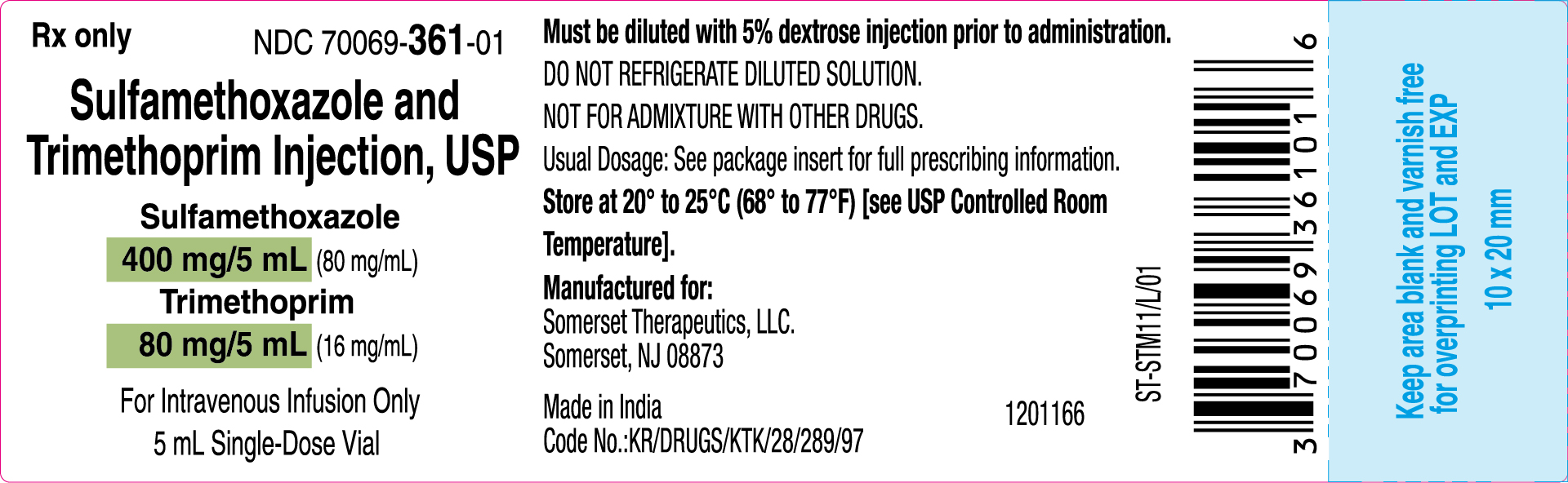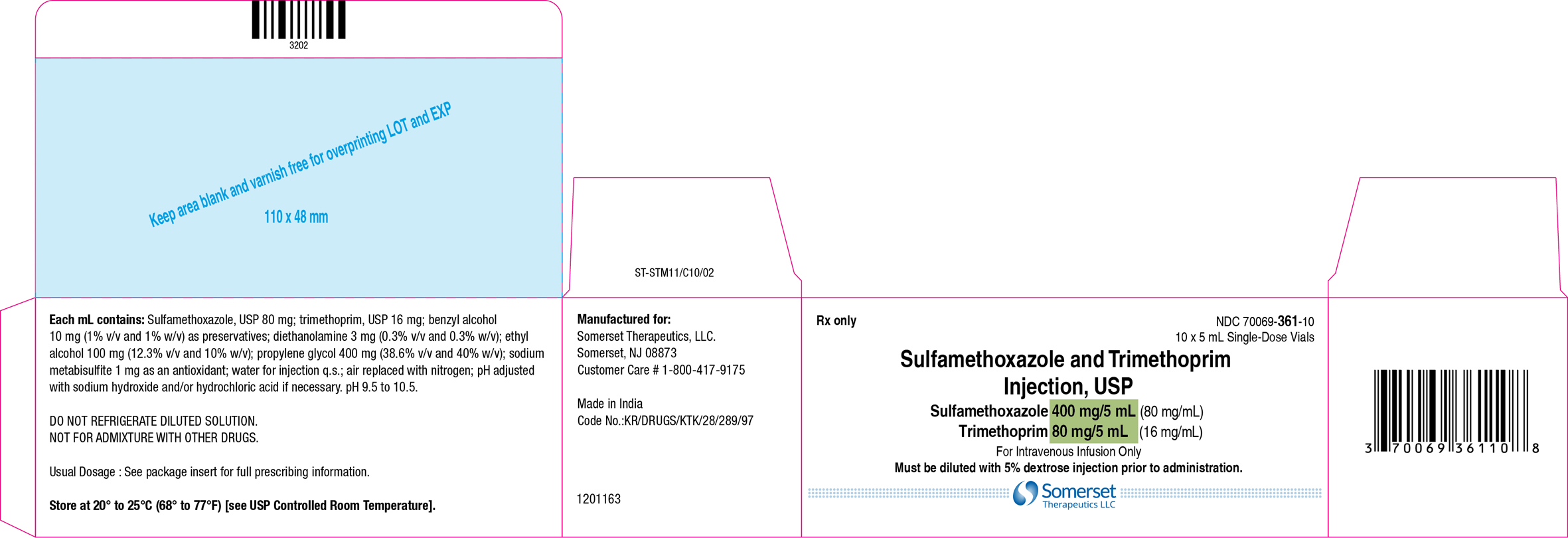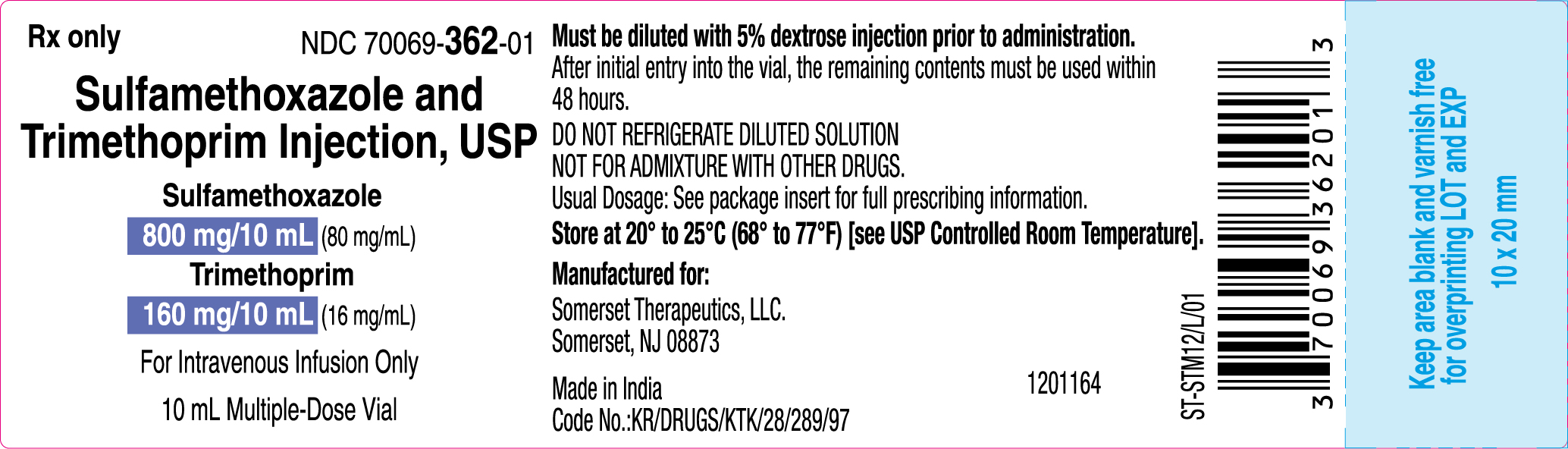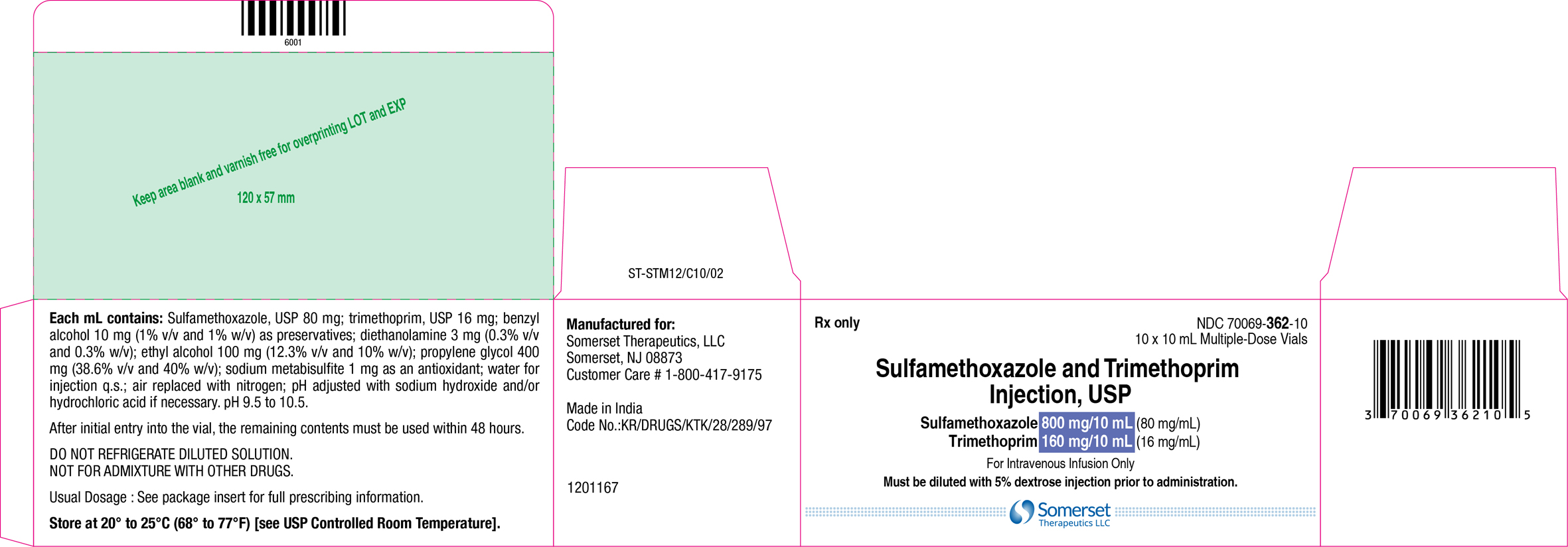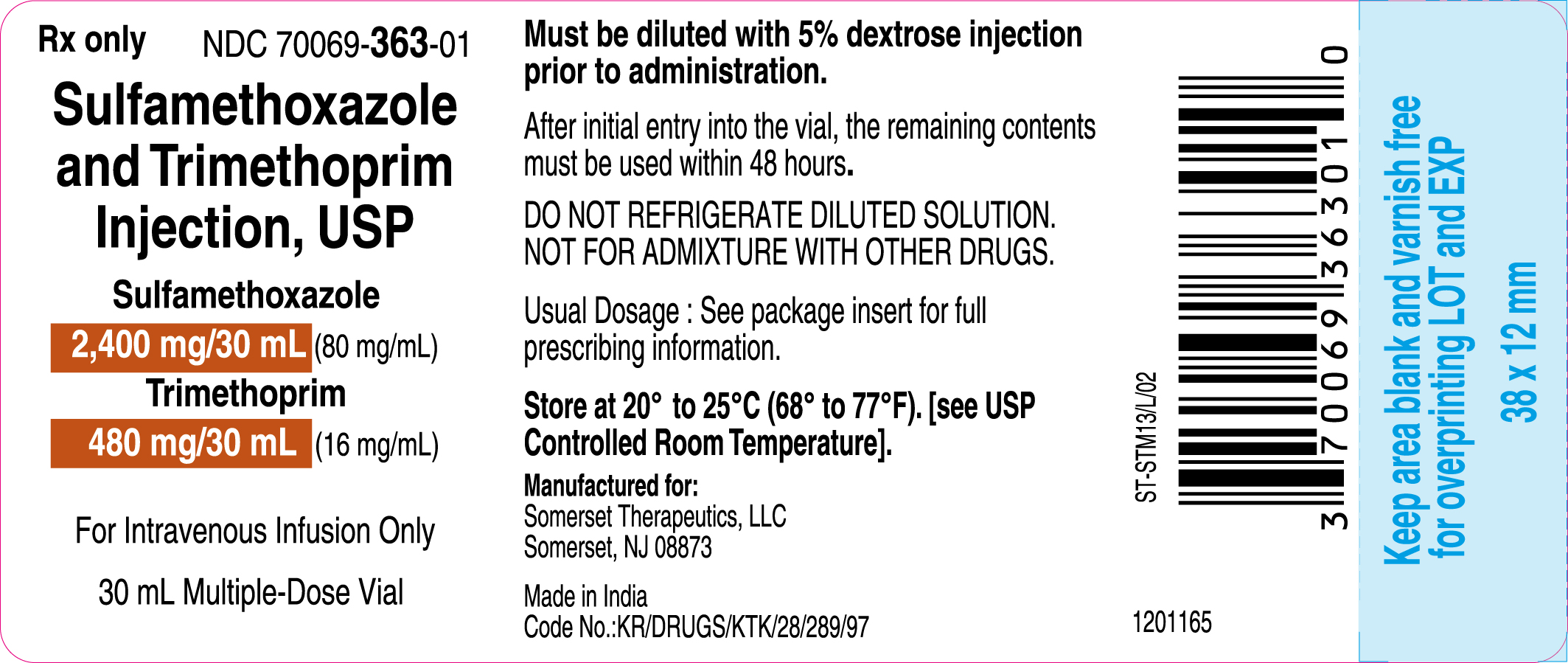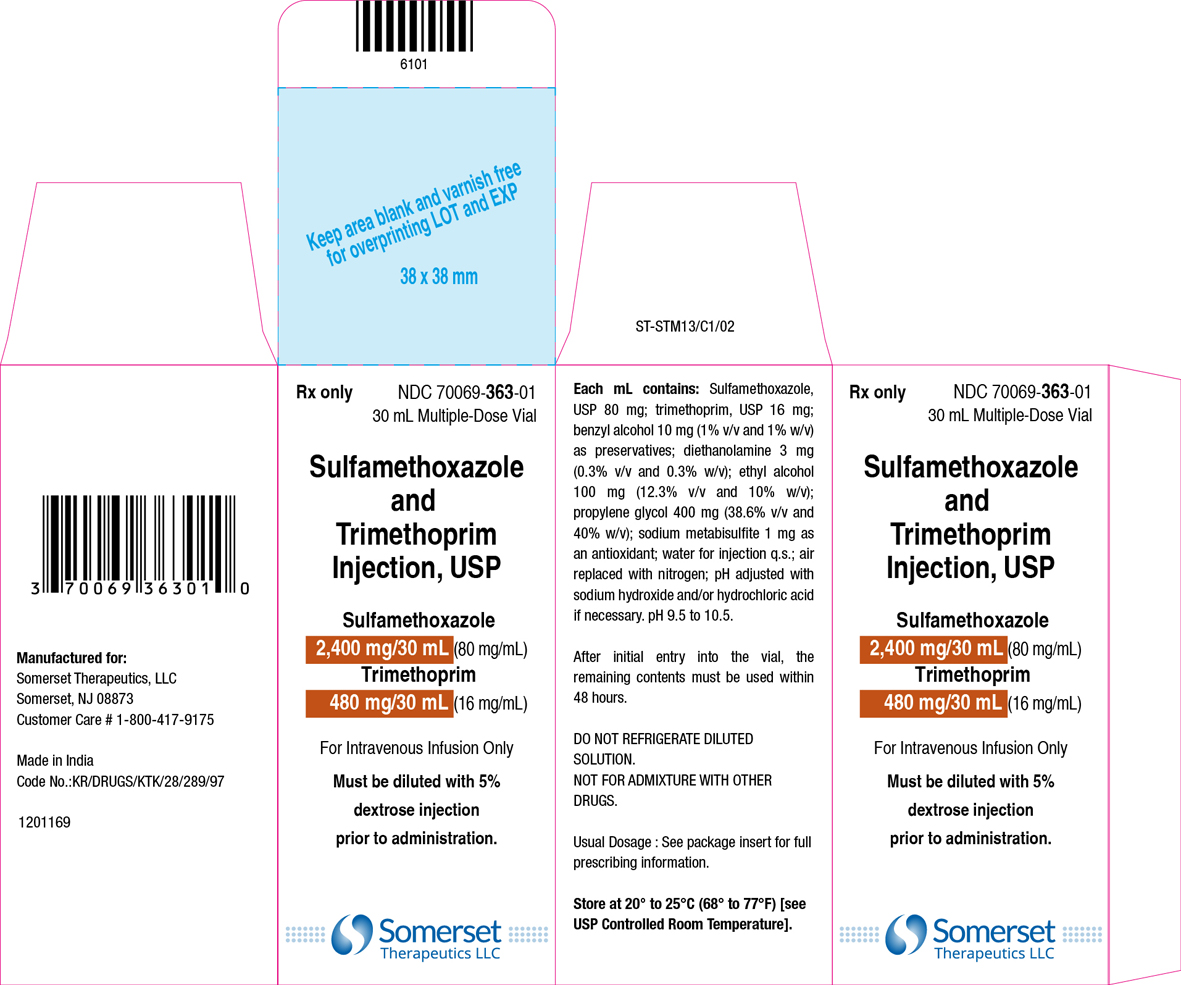 DRUG LABEL: Sulfamethoxazole and Trimethoprim
NDC: 70069-361 | Form: INJECTION, SOLUTION, CONCENTRATE
Manufacturer: Somerset Therapeutics, LLC
Category: prescription | Type: HUMAN PRESCRIPTION DRUG LABEL
Date: 20250716

ACTIVE INGREDIENTS: SULFAMETHOXAZOLE 80 mg/1 mL; TRIMETHOPRIM 16 mg/1 mL
INACTIVE INGREDIENTS: BENZYL ALCOHOL; DIETHANOLAMINE; ALCOHOL; PROPYLENE GLYCOL; SODIUM METABISULFITE; WATER; SODIUM HYDROXIDE; HYDROCHLORIC ACID

HIGHLIGHTS OF PRESCRIBING INFORMATION

These highlights do not include all the information needed to use SULFAMETHOXAZOLE AND TRIMETHOPRIM INJECTION safely and effectively. See full prescribing information for SULFAMETHOXAZOLE AND TRIMETHOPRIM INJECTION.
SULFAMETHOXAZOLE AND TRIMETHOPRIM injection, for intravenous use
Initial U.S. Approval: 1981

RECENT MAJOR CHANGES

Warnings and Precautions, Hemophagocytic Lymphohistiocytosis (5.3) | 02/2025

1 INDICATIONS AND USAGE

To reduce the development of drug-resistant bacteria and maintain the effectiveness of azithromycin and other antibacterial drugs, azithromycin should be used only to treat infections that are proven or strongly suspected to be caused by susceptible bacteria. When culture and susceptibility information are available, they should be considered in selecting or modifying antibacterial therapy. In the absence of such data, local epidemiology and susceptibility patterns may contribute to the empiric selection of therapy.

Azithromycin is a macrolide antibacterial drug indicated for the treatment of patients with mild to moderate infections caused by susceptible strains of the designated microorganisms in the specific conditions listed below. Recommended dosages and durations of therapy in adult and pediatric patient populations vary in these indications. [see Dosage and Administration (2)]

Azithromycin is a macrolide antibacterial drug indicated for mild to moderate infections caused by designated, susceptible bacteria:

macrolide antibacterial drug indicated for mild to moderate infections caused by designated, susceptible bacteria:

- Pneumocystis jirovecii Pneumonia (1.1)
- Shigellosis (1.2)
- Urinary Tract Infections (1.3)

To reduce the development of drug-resistant bacteria and maintain the effectiveness of Sulfamethoxazole and trimethoprim injection and other antibacterial drugs, Sulfamethoxazole and trimethoprim injection should be used only to treat or prevent infections that are proven or strongly suspected to be caused by susceptible bacteria. (1.4)

2 DOSAGE AND ADMINISTRATION

- For patients with impaired renal function, a reduced dosage should be employed. (2.2)
- Sulfamethoxazole and trimethoprim injection must be given by intravenous infusion over a period of 60 to 90 minutes. Rapid infusion or bolus injection must be avoided. (2.3)
- Sulfamethoxazole and trimethoprim injection must be diluted in 5% dextrose in water solution prior to administration. (2.4)
- Do not mix Sulfamethoxazole and trimethoprim injection with other drugs or solutions. (2.4)

3 DOSAGE FORMS AND STRENGTHS

Injection: 80 mg/mL sulfamethoxazole and 16 mg/mL trimethoprim in 5 mL single-dose, 10 mL and 30 mL multiple-dose vials. (3)

4 CONTRAINDICATIONS

- Known hypersensitivity to trimethoprim or sulfonamides (4)
- History of drug-induced immune thrombocytopenia with use of trimethoprim and/or sulfonamides (4)
- Documented megaloblastic anemia due to folate deficiency (4)
- Pediatric patients less than two months of age (4)
- Marked hepatic damage (4)
- Severe renal insufficiency when renal function status cannot be monitored (4)
- Concomitant administration with dofetilide (4)

5 WARNINGS AND PRECAUTIONS

- Embryo-fetal Toxicity: Increased risk of congenital malformations. Advise patient of the potential hazards to the fetus. (5.1)
- Hypersensitivity and Other Serious or Fatal Reactions: Discontinue at first appearance of skin rash or any sign of adverse reaction. (5.2)
- Hemophagocytic Lymphohistiocytosis (HLH): Cases of HLH have been reported in patients treated with sulfamethoxazole-trimethoprim. If HLH is suspected, discontinue sulfamethoxazole and trimethoprim injection immediately and institute appropriate management. (5.3)
- Thrombocytopenia: Monitor for hematologic toxicity. (5.4)
- Streptococcal Infections and Rheumatic Fever: Do not use for the treatment of group A beta-hemolytic streptococcal infections. (5.5)
- Clostridioides difficile- Associated Diarrhea: Evaluate if diarrhea occurs. (5.6)
- Sulfite Sensitivity: May cause allergic-type reactions. (5.7)
- Benzyl Alcohol Toxicity: Serious and fatal adverse reactions including "gasping syndrome" can occur in neonates. (5.8)
- Increased mortality with adjunctive leucovorin for Pneumocystis jiroveciipneumonia: Avoid concurrent use. (5.9)
- Propylene glycol toxicity: Hyperosmolarity with lactic or non-gap metabolic acidosis can occur. Monitor for total intake of propylene glycol and for acid-base disturbances. (5.10)

6 ADVERSE REACTIONS

The most common adverse effects are gastrointestinal disturbances (nausea, vomiting, and anorexia) and allergic skin reactions (such as rash and urticaria). (6)

To report SUSPECTED ADVERSE REACTIONS, contact Somerset Therapeutics, LLC at 1-800-417-9175 or FDA at 1-800-FDA-1088 or www.fda.gov/medwatch

7 DRUG INTERACTIONS

- CYP2C8, CYP2C9 or OCT2 substrates: Use with caution when co-administering with Sulfamethoxazole and trimethoprim injection. (7)
- Warfarin: Monitor prothrombin time and INR. (7)
- Phenytoin: Monitor serum phenytoin levels. (7)
- Digoxin: Concomitant use may increase digoxin blood levels, especially in elderly patients. Monitor serum digoxin levels. (7)
- Oral hypoglycemics: Concomitant use may potentiate hypoglycemic effects. Monitor blood glucose more frequently. (7)
- Zidovudine: Monitor for hematologic toxicity. (7)
- Procainamide: Monitor for signs of procainamide toxicity. (7)

8 USE IN SPECIFIC POPULATIONS

- Pregnancy: Sulfamethoxazole and trimethoprim injection may cause fetal harm to the fetus. Use only if potential benefit justifies potential risk to the fetus. (8.1)
- Lactation: Avoid breastfeeding during treatment with Sulfamethoxazole and trimethoprim injection because of potential risk of bilirubin displacement and kernicterus. (8.2)

FULL PRESCRIBING INFORMATION

1 INDICATIONS AND USAGE

1.1 Pneumocystis jirovecii Pneumonia

Limitation of Use:

Azithromycin should not be used in patients with pneumonia who are judged to be inappropriate for oral therapy because of moderate to severe illness or risk factors. (1.3)

To reduce the development of drug-resistant bacteria and maintain the effectiveness of azithromycin and other antibacterial drugs, azithromycin should be used only to treat infections that are proven or strongly suspected to be caused by susceptible bacteria

1.2 Shigellosis

Sulfamethoxazole and trimethoprim injection is indicated in the treatment of enteritis caused by susceptible strains of Shigella flexneri and Shigella sonnei in adults and pediatric patients two months of age and older.

1.3 Urinary Tract Infections

Sulfamethoxazole and trimethoprim injection is indicated in the treatment of severe or complicated urinary tract infections in adults and pediatric patients two months of age and older due to susceptible strains of Escherichia coli, Klebsiella species, Enterobacter species, Morganella morganii, Proteus mirabilis and Proteus vulgaris when oral administration of sulfamethoxazole and trimethoprim injection is not feasible and when the organism is not susceptible to single-agent antibacterials effective in the urinary tract.

1.4 Usage

To reduce the development of drug-resistant bacteria and maintain the effectiveness of sulfamethoxazole and trimethoprim injection and other antibacterial drugs, sulfamethoxazole and trimethoprim injection should be used only to treat or prevent infections that are proven or strongly suspected to be caused by susceptible bacteria. When culture and susceptibility information are available, they should be considered in selecting or modifying antibacterial therapy. In the absence of such data, local epidemiology and susceptibility patterns may contribute to empiric selection of therapy.

Although appropriate culture and susceptibility studies should be performed, therapy may be started while awaiting the results of these studies.

2 DOSAGE AND ADMINISTRATION

2.1 Dosage in Adults and Pediatric Patients (Two Months of Age and Older)

The maximum recommended daily dose is 60 mL (960 mg trimethoprim) per day.

Table 1: Dosage in Adults and Pediatric Patients (Two Months of Age and Older) by Indication

Dosage Guidelines
Infection | Total Daily Dose (based on trimethoprim content) | Frequency | Duration
Pneumocystis jirovecii Pneumonia* | 15-20 mg/kg (in 3 or 4 equally divided doses) | Every 6 to 8 hours | 14 days
Severe Urinary Tract Infections | 8-10 mg/kg (in 2 to 4 equally divided doses) | Every 6, 8 or 12 hours | 14 days
Shigellosis | 8-10 mg/kg (in 2 to 4 equally divided doses) | Every 6, 8 or 12 hours | 5 days

* A total daily dose of 10 to 15 mg/kg was sufficient in 10 adult patients with normal renal function in a published literature.^1

2.2 Dosage Modifications in Patients with Impaired Renal Function

When renal function is impaired, a reduced dosage should be employed, as shown in Table 2.

Table 2: Impaired Renal Function Dosage Guidelines

Creatinine Clearance (mL/min) | Recommended Dosage Regimen
Above 30 | Usual standard dosage regimen
15 – 30 | ½ the usual dosage regimen
Below 15 | Use not recommended

2.3 Important Administration Instructions

Administer the solution by intravenous infusion over a period of 60 to 90 minutes. Avoid administration by rapid infusion or bolus injection. Do NOT administer Sulfamethoxazole and trimethoprim injection intramuscularly.

Visually inspect parenteral drug products for particulate matter and discoloration prior to administration, whenever the solution and container permit.

2.4 Method of Preparation

Dilution of Single- and Multiple-Dose Vials

Sulfamethoxazole and trimethoprim injection must be diluted. Each 5 mL should be added to 125 mL of 5% dextrose in water. After diluting with 5% dextrose in water, the solution should not be refrigerated and should be used within 6 hours.

If a dilution of 5 mL per 100 mL of 5% dextrose in water is desired, it should be used within 4 hours. In those instances where fluid restriction is desirable, each 5 mL may be added to 75 mL of 5% dextrose in water. Under these circumstances the solution should be mixed just prior to use and should be administered within 2 hours.

If upon visual inspection there is cloudiness or evidence of crystallization after mixing, the solution should be discarded and a fresh solution prepared.

Do NOT mix sulfamethoxazole and trimethoprim injection in 5% dextrose in water with drugs or solutions in the same container.

Multiple-dose Vials (Handling)

After initial entry into the vial, the remaining contents must be used within 48 hours.

Infusion Systems for Intravenous Administration

The following infusion systems have been tested and found satisfactory: unit-dose glass containers; unit-dose polyvinyl chloride and polyolefin containers. No other systems have been tested and therefore no others can be recommended.

3 DOSAGE FORMS AND STRENGTHS

Sulfamethoxazole and trimethoprim injection, USP is available as an injection containing 80 mg/mL of sulfamethoxazole and 16 mg/mL of trimethoprim in 5 mL single-dose, 10 mL and 30 mL multiple-dose vials.

4 CONTRAINDICATIONS

Sulfamethoxazole and trimethoprim injection is contraindicated in the following situations:

- Known hypersensitivity to trimethoprim or sulfonamides [see Warnings and Precautions (5.2)]
- History of drug-induced immune thrombocytopenia with use of trimethoprim and/or sulfonamides [see Warnings and Precautions (5.4)]
- Documented megaloblastic anemia due to folate deficiency [see Warnings and Precautions (5.11)]
- Pediatric patients less than two months of age [see Use in Specific Populations (8.4)]
- Marked hepatic damage [see Warnings and Precautions (5.11, 5.14)]
- Severe renal insufficiency when renal function status cannot be monitored [see Warnings and Precautions (5.11, 5.14)]
- Concomitant administration with dofetilide^2,3 [see Drug Interactions (7)]

5 WARNINGS AND PRECAUTIONS

5.1 Embryo-fetal Toxicity

Some epidemiologic studies suggest that exposure to sulfamethoxazole and trimethoprim injection during pregnancy may be associated with an increased risk of congenital malformations, particularly neural tube defects, cardiovascular malformations, urinary tract defects, oral clefts, and club foot. If sulfamethoxazole and trimethoprim injection is used during pregnancy, or if the patient becomes pregnant while taking this drug, the patient should be advised of the potential hazards to the fetus [see Use in Specific Populations (8.1)].

5.2 Hypersensitivity and Other Serious or Fatal Reactions

Fatalities and serious adverse reactions including severe cutaneous adverse reactions (SCARs), including Stevens-Johnson Syndrome, toxic epidermal necrolysis, drug reaction with eosinophilia and systemic symptoms (DRESS), acute febrile neutrophilic dermatosis (AFND), acute generalized erythematous pustulosis (AGEP); fulminant hepatic necrosis; agranulocytosis, aplastic anemia and other blood dyscrasias; acute and delayed lung injury; anaphylaxis and circulatory shock have occurred with the administration of sulfamethoxazole and trimethoprim products, including sulfamethoxazole and trimethoprim injection [see Adverse Reactions (6.1)].

Cough, shortness of breath and pulmonary infiltrates potentially representing hypersensitivity reactions of the respiratory tract have been reported in association with sulfamethoxazole and trimethoprim treatment.

Other severe pulmonary adverse reactions occurring within days to week of sulfamethoxazole and trimethoprim injection initiation and resulting in prolonged respiratory failure requiring mechanical ventilation or extracorporeal membrane oxygenation (ECMO), lung transplantation or death have also been reported in patients and otherwise healthy individuals treated with sulfamethoxazole and trimethoprim products.

Circulatory shock with fever, severe hypotension, and confusion requiring intravenous fluid resuscitation and vasopressors has occurred within minutes to hours of re-challenge with sulfamethoxazole and trimethoprim products, including sulfamethoxazole and trimethoprim injection, in patients with history of recent (days to weeks) exposure to sulfamethoxazole and trimethoprim.

Sulfamethoxazole and trimethoprim injection should be discontinued at the first appearance of skin rash or any sign of a serious adverse reaction. A skin rash may be followed by more severe reactions, such as Stevens-Johnson syndrome, toxic epidermal necrolysis, DRESS, AFND, AGEP, hepatic necrosis or serious blood disorder. Clinical signs, such as rash, pharyngitis, fever, arthralgia, cough, chest pain, dyspnea, pallor, purpura or jaundice may be early indications of serious reactions.

5.3 Hemophagocytic Lymphohistiocytosis

Cases of hemophagocytic lymphohistiocytosis (HLH) have been reported in patients treated with sulfamethoxazole-trimethoprim. HLH is a life-threatening syndrome of pathologic immune activation characterized by clinical signs and symptoms of extreme systemic inflammation. Signs and symptoms of HLH may include fever, hepatosplenomegaly, rash, lymphadenopathy, neurologic symptoms, cytopenias, high serum ferritin, hypertriglyceridemia, and liver enzyme and coagulation abnormalities. If HLH is suspected, discontinue sulfamethoxazole and trimethoprim injection immediately and institute appropriate management.

5.4 Thrombocytopenia

Sulfamethoxazole and trimethoprim injection-induced thrombocytopenia may be an immune-mediated disorder. Severe cases of thrombocytopenia that are fatal or life threatening have been reported. Monitor patients for hematologic toxicity. Thrombocytopenia usually resolves within a week upon discontinuation of sulfamethoxazole and trimethoprim injection.

5.5 Streptococcal Infections and Rheumatic Fever

Avoid use of sulfamethoxazole and trimethoprim injection in the treatment of streptococcal pharyngitis. Clinical studies have documented that patients with group A β-hemolytic streptococcal tonsillopharyngitis have a greater incidence of bacteriologic failure when treated with sulfamethoxazole and trimethoprim injection than do those patients treated with penicillin, as evidenced by failure to eradicate this organism from the tonsillopharyngeal area. Therefore, sulfamethoxazole and trimethoprim injection will not prevent sequelae such as rheumatic fever.

5.6 Clostridioides difficile-Associated Diarrhea

Clostridioides difficile associated diarrhea (CDAD) has been reported with use of nearly all antibacterial agents, including sulfamethoxazole and trimethoprim injection, and may range in severity from mild diarrhea to fatal colitis. Treatment with antibacterial agents alters the normal flora of the colon leading to overgrowth of C. difficile.

C. difficile produces toxins A and B which contribute to the development of CDAD. Hypertoxin producing strains of C. difficile cause increased morbidity and mortality, as these infections can be refractory to antimicrobial therapy and may require colectomy. CDAD must be considered in all patients who present with diarrhea following antibacterial use. Careful medical history is necessary since CDAD has been reported to occur over two months after the administration of antibacterial agents.

If CDAD is suspected or confirmed, ongoing antibacterial use not directed against C. difficile may need to be discontinued. Appropriate fluid and electrolyte management, protein supplementation, antibacterial treatment of C. difficile, and surgical evaluation should be instituted as clinically indicated.

5.7 Sulfite Sensitivity

Sulfamethoxazole and trimethoprim injection contains sodium metabisulfite, a sulfite that may cause allergic-type reactions, including anaphylactic symptoms and life-threatening or less severe asthmatic episodes in certain susceptible people. The overall prevalence of sulfite sensitivity in the general population is unknown. Sulfite sensitivity is seen more frequently in asthmatic than in non-asthmatic people.

5.8 Benzyl Alcohol Toxicity in Pediatric Patients ("Gasping Syndrome")

Sulfamethoxazole and trimethoprim injection contains benzyl alcohol as a preservative. Serious and fatal adverse reactions including "gasping syndrome" can occur in neonates and low birth weight infants treated with benzyl alcohol-preserved formulations in infusion solutions, including sulfamethoxazole and trimethoprim injection. The "gasping syndrome" is characterized by central nervous system depression, metabolic acidosis, and gasping respirations. Sulfamethoxazole and trimethoprim injection is contraindicated in pediatric patients less than two months of age [see Contraindications (4)].

When prescribing sulfamethoxazole and trimethoprim injection in pediatric patients (two months of age and older), consider the combined daily metabolic load of benzyl alcohol from all sources including sulfamethoxazole and trimethoprim injection (contains 10 mg of benzyl alcohol per mL) and other drugs containing benzyl alcohol. The minimum amount of benzyl alcohol at which serious adverse reactions may occur is not known [see Use in Specific Populations (8.4)].

5.9 Risk Associated with Concurrent Use of Leucovorin for Pneumocystis jirovecii Pneumonia

Treatment failure and excess mortality were observed when sulfamethoxazole and trimethoprim injection was used concomitantly with leucovorin for the treatment of HIV positive patients with P. jirovecii pneumonia in a randomized placebo -controlled trial.^4 Avoid coadministration of sulfamethoxazole and trimethoprim injection and leucovorin during treatment of P. jirovecii pneumonia.

5.10 Propylene Glycol Toxicity

Sulfamethoxazole and trimethoprim injection contains propylene glycol as a solvent (40% v/v). When administered at high doses as for the treatment of P. jirovecii pneumonia and concomitantly with other products that contain propylene glycol, hyperosmolarity with anion gap metabolic acidosis, including lactic acidosis can occur. Propylene glycol toxicity can lead to acute kidney injury, CNS toxicity, and multi-organ failure. Monitor for the total daily intake of propylene glycol from all sources and for acid-base disturbances. Discontinue sulfamethoxazole and trimethoprim injection if propylene glycol toxicity is suspected [see Adverse Reactions (6)].

5.11 Folate Deficiency

Avoid use of sulfamethoxazole and trimethoprim injection in patients with impaired renal or hepatic function, in those with possible folate deficiency (e.g., the elderly, chronic alcoholics, patients receiving anticonvulsant therapy, patients with malabsorption syndrome, and patients in malnutrition states) and in those with severe allergies or bronchial asthma.

Hematologic changes indicative of folic acid deficiency may occur in elderly patients or in patients with preexisting folic acid deficiency or kidney failure. These effects are reversible by folinic acid therapy [see Use in Specific Populations (8.5)].

5.12 Hemolysis

In glucose-6-phosphate dehydrogenase deficient individuals, hemolysis may occur. This reaction is frequently dose-related.

5.13 Infusion Reactions

Local irritation and inflammation due to extravascular infiltration of the infusion have been observed with sulfamethoxazole and trimethoprim injection. If these occur the infusion should be discontinued and restarted at another site.

5.14 Hypoglycemia

Cases of hypoglycemia in non-diabetic patients treated with sulfamethoxazole and trimethoprim injection have been seen, usually occurring after a few days of therapy. Patients with renal dysfunction, liver disease, malnutrition or those receiving high doses of sulfamethoxazole and trimethoprim injection are particularly at risk.

5.15 Impaired Phenylalanine Metabolism

Trimethoprim, component of sulfamethoxazole and trimethoprim injection, has been noted to impair phenylalanine metabolism, but this is of no significance in phenylketonuric patients on appropriate dietary restriction.

5.16 Porphyria and Hypothyroidism

Like other drugs containing sulfonamides, sulfamethoxazole and trimethoprim injection can precipitate porphyria crisis and hypothyroidism. Avoid use of sulfamethoxazole and trimethoprim injection in patients with porphyria or thyroid dysfunction.

5.17 Potential Risk in the Treatment of Pneumocystis jirovecii Pneumonia in Patients with Acquired Immunodeficiency Syndrome (AIDS)

AIDS patients may not tolerate or respond to sulfamethoxazole and trimethoprim injection in the same manner as non-AIDS patients. The incidence of adverse reactions, particularly rash, fever, leukopenia, and elevated aminotransferase (transaminase) values, with sulfamethoxazole and trimethoprim injection therapy in AIDS patients who are being treated for P. jirovecii pneumonia has been reported to be increased compared with the incidence normally associated with the use of sulfamethoxazole and trimethoprim injection in non-AIDS patients. If a patient develops skin rash, fever, leukopenia or any sign of an adverse reaction, reevaluate benefit-risk of continuing therapy or re-challenge with sulfamethoxazole and trimethoprim injection [see Warnings and Precautions (5.2)].

Avoid coadministration of sulfamethoxazole and trimethoprim injection and leucovorin during treatment of Pneumocystis jirovecii pneumonia [see Warnings and Precautions (5.9)]

5.18 Electrolyte Abnormalities

Hyperkalemia

High dosage of trimethoprim, as used in patients with P. jirovecii pneumonia, induces a progressive but reversible increase of serum potassium concentrations in a substantial number of patients. Even treatment with recommended doses may cause hyperkalemia when trimethoprim is administered to patients with underlying disorders of potassium metabolism, with renal insufficiency, or if drugs known to induce hyperkalemia are given concomitantly. Close monitoring of serum potassium is warranted in these patients.

Hyponatremia

Severe and symptomatic hyponatremia can occur in patients receiving sulfamethoxazole and trimethoprim injection, particularly for the treatment of P. jirovecii pneumonia. Evaluation for hyponatremia and appropriate correction is necessary in symptomatic patients to prevent life-threatening complications.

Crystalluria

During treatment, ensure adequate fluid intake and urinary output to prevent crystalluria. Patients who are "slow acetylators" may be more prone to idiosyncratic reactions to sulfonamides.

5.19 Monitoring of Laboratory Tests

Complete blood counts and clinical chemistry testing should be done frequently in patients receiving sulfamethoxazole and trimethoprim injection. Discontinue sulfamethoxazole and trimethoprim injection if a significant electrolyte abnormality, renal insufficiency or reduction in the count of any formed blood element is noted. Perform urinalyses with careful microscopic examination and renal function tests during therapy, particularly for those patients with impaired renal function.

5.20 Development of Drug-Resistant Bacteria

Prescribing sulfamethoxazole and trimethoprim injection in the absence of a proven or strongly suspected bacterial infection or a prophylactic indication is unlikely to provide benefit to the patient and increases the risk of the development of drug-resistant bacteria.

6 ADVERSE REACTIONS

The following serious adverse reactions are described elsewhere in the labeling:

- Embryo-fetal Toxicity [see Warnings and Precautions (5.1)]
- Hypersensitivity and Other Serious or Fatal Reactions [see Warnings and Precautions (5.2)]
- Thrombocytopenia [see Warnings and Precautions (5.4)]
- Clostridioides difficile-Associated Diarrhea [see Warnings and Precautions (5.6)]
- Sulfite Sensitivity [see Warnings and Precautions (5.7)]
- Risk Associated with Concurrent Use of Leucovorin for Pneumocystis jiroveciiPneumonia [see Warnings and Precautions (5.9)]
- Propylene Glycol Toxicity [see Warnings and Precautions (5.10)]
- Infusion Reactions [see Warnings and Precautions (5.13)]
- Hypoglycemia [see Warnings and Precautions (5.14)]
- Electrolyte Abnormalities [see Warnings and Precautions (5.18)]

6.1 Clinical Trials Experience

The following adverse reactions associated with the use of sulfamethoxazole and trimethoprim injection or sulfamethoxazole and trimethoprim were identified in clinical trials, postmarketing or published reports. Because some of these reactions were reported voluntarily from a population of uncertain size, it is not always possible to reliably estimate their frequency or establish a causal relationship to drug exposure.

The most common adverse reactions are gastrointestinal disturbances (nausea, vomiting, and anorexia) and allergic skin reactions (such as rash and urticaria).

Fatalities and serious adverse reactions, including severe cutaneous adverse reactions (SCARs), including Stevens-Johnson syndrome, toxic epidermal necrolysis, drug reaction with eosinophilia and systemic symptoms (DRESS), acute febrile neutrophilic dermatosis (AFND), acute generalized erythematous pustulosis (AGEP); fulminant hepatic necrosis; agranulocytosis, aplastic anemia and other blood dyscrasias; acute and delayed lung injury; anaphylaxis and circulatory shock have occurred with the administration of sulfamethoxazole and trimethoprim products, including sulfamethoxazole and trimethoprim injection [see Warnings and Precautions (5.2)].

Local reaction, pain and slight irritation on intravenous (IV) administration are infrequent. Thrombophlebitis has been observed.

Table 3: Adverse Reactions Reported with Sulfamethoxazole and trimethoprim injection

Body System | Adverse Reactions
Hematologic | Agranulocytosis, aplastic anemia, thrombocytopenia, leukopenia, neutropenia, hemolytic anemia, megaloblastic anemia, hypoprothrombinemia, methemoglobinemia, eosinophilia, thrombotic thrombocytopenic purpura, idiopathic thrombocytopenic purpura.
Allergic / Immune Reactions | Stevens-Johnson syndrome, toxic epidermal necrolysis, anaphylaxis, allergic myocarditis, erythema multiforme, exfoliative dermatitis, angioedema, drug fever, chills, Henoch-Schoenlein purpura, serum sickness-like syndrome, generalized allergic reactions, generalized skin eruptions, photosensitivity, conjunctival and scleral injection, pruritus, urticaria, rash, periarteritis nodosa, hemophagocytic lymphohistiocytosis (HLH), systemic lupus erythematosus, drug reaction with eosinophilia and systemic symptoms (DRESS), acute generalized erythematous pustulosis (AGEP), and acute febrile neutrophilic dermatosis (AFND) [see Warnings and Precautions (5.2 and 5.3)].
Gastrointestinal | Hepatitis (including cholestatic jaundice and hepatic necrosis), elevation of serum transaminase and bilirubin, pseudomembranous enterocolitis, pancreatitis, stomatitis, glossitis, nausea, emesis, abdominal pain, diarrhea, anorexia.
Genitourinary | Renal failure, interstitial nephritis, BUN and serum creatinine elevation, renal insufficiency, oliguria and anuria, crystalluria and nephrotoxicity in association with cyclosporine.
Metabolic and Nutritional | Hyperkalemia, hyponatremia [see Warnings and Precautions (5.18)] , metabolic acidosis.
Neurologic | Aseptic meningitis, convulsions, peripheral neuritis, ataxia, vertigo, tinnitus, headache.
Psychiatric | Hallucinations, depression, apathy, nervousness.
Endocrine | The sulfonamides bear certain chemical similarities to some goitrogens, diuretics (acetazolamide and the thiazides) and oral hypoglycemic agents. Cross-sensitivity may exist with these agents. Diuresis and hypoglycemia have occurred.
Musculoskeletal | Arthralgia, myalgia, rhabdomyolysis.
Respiratory | Cough, shortness of breath and pulmonary infiltrates, acute eosinophilic pneumonia, acute and delayed lung injury, interstitial lung disease, acute respiratory failure [see Warnings and Precautions (5.2)] .
Cardiovascular System | QT prolongation resulting in ventricular tachycardia and torsades de pointes, circulatory shock [see Warnings and Precautions (5.2)].
Miscellaneous | Weakness, fatigue, insomnia.

7 DRUG INTERACTIONS

Potential for Sulfamethoxazole and trimethoprim injection to Affect Other Drugs

Trimethoprim is an inhibitor of CYP2C8 as well as OCT2 transporter. Sulfamethoxazole is an inhibitor of CYP2C9. Avoid coadministration of sulfamethoxazole and trimethoprim injection with drugs that are substrates of CYP2C8 and 2C9 or OCT2.

Table 4: Drug Interactions with Sulfamethoxazole and trimethoprim injection

Drug(s) | Recommendation | Comments
Diuretics | Avoid concurrent use | In elderly patients concurrently receiving certain diuretics, primarily thiazides, an increased incidence of thrombocytopenia with purpura has been reported.
Warfarin | Monitor prothrombin time and INR | It has been reported that sulfamethoxazole and trimethoprim injection may prolong the prothrombin time in patients who are receiving the anticoagulant warfarin (a CYP2C9 substrate). This interaction should be kept in mind when sulfamethoxazole and trimethoprim injection is given to patients already on anticoagulant therapy, and the coagulation time should be reassessed.
Phenytoin | Monitor serum phenytoin levels | Sulfamethoxazole and trimethoprim injection may inhibit the hepatic metabolism of phenytoin (a CYP2C9 substrate). Sulfamethoxazole and trimethoprim injection, given at a common clinical dosage, increased the phenytoin half-life by 39% and decreased the phenytoin metabolic clearance rate by 27%. When administering these drugs concurrently, one should be alert for possible excessive phenytoin effect.
Methotrexate | Avoid concurrent use | Sulfonamides can also displace methotrexate from plasma protein binding sites and can compete with the renal transport of methotrexate, thus increasing free methotrexate concentrations.
Cyclosporine | Avoid concurrent use | There have been reports of marked but reversible nephrotoxicity with coadministration of sulfamethoxazole and trimethoprim injection and cyclosporine in renal transplant recipients.
Digoxin | Monitor serum digoxin levels | Increased digoxin blood levels can occur with concomitant sulfamethoxazole and trimethoprim injection therapy, especially in elderly patients
Indomethacin | Avoid concurrent use | Increased sulfamethoxazole blood levels may occur in patients who are also receiving indomethacin.
Pyrimethamine | Avoid concurrent use | Occasional reports suggest that patients receiving pyrimethamine as malaria prophylaxis in doses exceeding 25 mg weekly may develop megaloblastic anemia if sulfamethoxazole and trimethoprim injection is prescribed.
Tricyclic Antidepressants (TCAs) | Monitor therapeutic response and adjust dose of TCA accordingly | The efficacy of tricyclic antidepressants can decrease when coadministered with sulfamethoxazole and trimethoprim injection.
Oral hypoglycemics | Monitor blood glucose more frequently | Like other sulfonamide-containing drugs, sulfamethoxazole and trimethoprim injection potentiates the effect of oral hypoglycemic that are metabolized by CYP2C8 (e.g., pioglitazone, repaglinide, and rosiglitazone) or CYP2C9 (e.g., glipizide and glyburide) or eliminated renally via OCT2 (e.g., metformin). Additional monitoring of blood glucose may be warranted.
Amantadine | Avoid concurrent use | In the literature, a single case of toxic delirium has been reported after concomitant intake of sulfamethoxazole and trimethoprim injection and amantadine (an OCT2 substrate). Cases of interactions with other OCT2 substrates, memantine and metformin, have also been reported.
Angiotensin Converting Enzyme Inhibitors | Avoid concurrent use | In the literature, three cases of hyperkalemia in elderly patients have been reported after concomitant intake of sulfamethoxazole and trimethoprim injection and an angiotensin converting enzyme inhibitor.^6,7
Zidovudine | Monitor for hematologic toxicity | Zidovudine and sulfamethoxazole and trimethoprim injection are known to induce hematological abnormalities. Hence, there is potential for an additive myelotoxicity when coadministered.^8
Dofetilide | Concurrent administration is contraindicated | Elevated plasma concentrations of dofetilide have been reported following concurrent administration of trimethoprim and dofetilide. Increased plasma concentrations of dofetilide may cause serious ventricular arrhythmias associated with QT interval prolongation, including torsade de pointes .^2,3
Procainamide | Closely monitor for clinical and ECG signs of procainamide toxicity and/or procainamide plasma concentration if available | Trimethoprim increases the plasma concentrations of procainamide and its active N-acetyl metabolite (NAPA) when trimethoprim and procainamide are coadministered. The increased procainamide and NAPA plasma concentrations that resulted from the pharmacokinetic interaction with trimethoprim are associated with further prolongation of the QTc interval.^9

7.1 Interactions with Laboratory or Diagnostic Testing

Sulfamethoxazole and trimethoprim injection, specifically the trimethoprim component, can interfere with a serum methotrexate assay as determined by the competitive binding protein technique (CBPA) when a bacterial dihydrofolate reductase is used as the binding protein. No interference occurs, however, if methotrexate is measured by a radioimmunoassay (RIA).

The presence of sulfamethoxazole and trimethoprim injection may also interfere with the Jaff¡SR alkaline picrate reaction assay for creatinine, resulting in overestimations of about 10% in the range of normal values.

8 USE IN SPECIFIC POPULATIONS

8.1 Pregnancy

Risk Summary

Sulfamethoxazole and trimethoprim injection may cause fetal harm if administered to a pregnant woman. Some epidemiologic studies suggest that exposure to sulfamethoxazole and trimethoprim injection during pregnancy may be associated with an increased risk of congenital malformations, particularly neural tube defects, cardiovascular abnormalities, urinary tract defects, oral clefts, and club foot (see Human Data).

One of 3 rat studies showed cleft palate at doses approximately 5 times the recommended human dose on a body surface area basis; the other 2 studies did not show teratogenicity at similar doses. Studies in pregnant rabbits showed increased fetal loss at approximately 6 times the human dose on a body surface area basis (see Animal Data).

The estimated background risk of major birth defects and miscarriages for the indicated population is unknown. In the U.S. general population, the estimated background risk of major birth defects and miscarriage in clinically recognized pregnancies is 2% to 4% and 15% to 20%, respectively. Advise pregnant women of the potential harm of sulfamethoxazole and trimethoprim injection to the fetus (see Clinical Considerations).

Clinical Considerations

Disease-associated Maternal and/or Embryo/Fetal Risk

Urinary tract infection in pregnancy is associated with adverse perinatal outcomes such as preterm birth, low birth weight, and pre-eclampsia, and increased mortality to the pregnant woman. P. jirovecii pneumonia in pregnancy is associated with preterm birth and increased morbidity and mortality for the pregnant woman. Sulfamethoxazole and trimethoprim injection should be used during pregnancy only if the potential benefit justifies the potential risk to the fetus.

Data

Human Data

While there are no large, prospective, well-controlled studies in pregnant women and their babies, some retrospective epidemiologic studies suggest an association between first trimester exposure to sulfamethoxazole and trimethoprim injection with an increased risk of congenital malformations, particularly neural tube defects, cardiovascular abnormalities, urinary tract defects, oral clefts, and club foot. These studies, however, were limited by the small number of exposed cases and the lack of adjustment for multiple statistical comparisons and confounders. These studies are further limited by recall, selection, and information biases, and by limited generalizability of their findings. Lastly, outcome measures varied between studies, limiting cross-study comparisons.

Alternatively, other epidemiologic studies did not detect statistically significant associations between sulfamethoxazole and trimethoprim injection exposure and specific malformations. Brumfitt and Pursell,^10 in a retrospective study, reported the outcome of 186 pregnancies during which the mother received either placebo or oral trimethoprim and sulfamethoxazole. The incidence of congenital abnormalities was 4.5% (3 of 66) in those who received placebo and 3.3% (4 of 120) in those receiving trimethoprim and sulfamethoxazole. There were no abnormalities in the 10 children whose mothers received the drug during the first trimester. In a separate survey, Brumfitt and Pursell also found no congenital abnormalities in 35 children whose mothers had received oral trimethoprim and sulfamethoxazole at the time of conception or shortly thereafter.

Animal Data

In rats, oral doses of either 533 mg/kg sulfamethoxazole or 200 mg/kg trimethoprim produced teratologic effects manifested mainly as cleft palates. These doses are approximately 5 and 6 times the recommended human total daily dose on a body surface area basis. In two studies in rats, no teratology was observed when 512 mg/kg of sulfamethoxazole was used in combination with 128 mg/kg of trimethoprim. In some rabbit studies, an overall increase in fetal loss (dead and resorbed conceptuses) was associated with doses of trimethoprim 6 times the human therapeutic dose based on body surface area.

8.2 Lactation

Risk Summary

Levels of sulfamethoxazole and trimethoprim injection in breast milk are approximately 2 to 5% of the recommended daily dose for pediatric patients over two months of age. There is no information regarding the effect of sulfamethoxazole and trimethoprim injection on the breastfed infant or the effect on milk production. Because of the potential risk of bilirubin displacement and kernicterus on the breastfed child [see Contraindications (4)], advise women to avoid breastfeeding during treatment with sulfamethoxazole and trimethoprim injection.

8.4 Pediatric Use

Sulfamethoxazole and trimethoprim injection is contraindicated in pediatric patients younger than two months of age because of the potential risk of bilirubin displacement and kernicterus [see Contraindications (4)].

Serious adverse reactions including fatal reactions and the "gasping syndrome" occurred in premature neonates and low birth weight infants in the neonatal intensive care unit who received benzyl alcohol as a preservative in infusion solutions. In these cases, benzyl alcohol dosages of 99 to 234 mg/kg/day produced high levels of benzyl alcohol and its metabolites in the blood and urine (blood levels of benzyl alcohol were 0.61 to 1.378 mmol/L). Additional adverse reactions included gradual neurological deterioration, seizures, intracranial hemorrhage, hematologic abnormalities, skin breakdown, hepatic and renal failure, hypotension, bradycardia, and cardiovascular collapse. Preterm, low-birth weight infants may be more likely to develop these reactions because they may be less able to metabolize benzyl alcohol.

When prescribing sulfamethoxazole and trimethoprim injection in pediatric patients consider the combined daily metabolic load of benzyl alcohol from all sources including sulfamethoxazole and trimethoprim injection (Sulfamethoxazole and trimethoprim injection contains 10 mg of benzyl alcohol per mL) and other drugs containing benzyl alcohol. The minimum amount of benzyl alcohol at which serious adverse reactions may occur is not known [see Warnings and Precautions (5.8)].

8.5 Geriatric Use

Clinical studies of sulfamethoxazole and trimethoprim injection did not include sufficient numbers of subjects aged 65 and over to determine whether they respond differently from younger subjects.

There may be an increased risk of severe adverse reactions in elderly patients, particularly when complicating conditions exist, e.g., impaired kidney and/or liver function, or concomitant use of other drugs. Severe skin reactions, generalized bone marrow suppression [see Warnings and Precautions (5.11), Adverse Reactions (6.1)], a specific decrease in platelets (with or without purpura), and hyperkalemia are the most frequently reported severe adverse reactions in elderly patients.

In those concurrently receiving certain diuretics, primarily thiazides, an increased incidence of thrombocytopenia with purpura has been reported. Increased digoxin blood levels can occur with concomitant sulfamethoxazole and trimethoprim injection therapy, especially in elderly patients. Serum digoxin levels should be monitored [see Drug Interactions (7)].

Hematologic changes indicative of folic acid deficiency may occur in elderly patients. These effects are reversible by folinic acid therapy. Appropriate dosage adjustments should be made for patients with impaired kidney function and duration of use should be as short as possible to minimize risks of undesired reactions [see Dosage and Administration (2.2)].

The trimethoprim component of sulfamethoxazole and trimethoprim injection may cause hyperkalemia when administered to patients with underlying disorders of potassium metabolism, with renal insufficiency or when given concomitantly with drugs known to induce hyperkalemia, such as angiotensin converting enzyme inhibitors. Close monitoring of serum potassium is warranted in these patients. Discontinuation of sulfamethoxazole and trimethoprim injection treatment is recommended to help lower potassium serum levels.

Pharmacokinetics parameters for sulfamethoxazole were similar for geriatric subjects and younger adult subjects. The mean maximum serum trimethoprim concentration was higher and mean renal clearance of trimethoprim was lower in geriatric subjects compared with younger subjects [see Clinical Pharmacology (12.3)].

10 OVERDOSAGE

Acute

Since there has been no extensive experience in humans with single doses of sulfamethoxazole and trimethoprim injection in excess of 25 mL (400 mg trimethoprim and 2000 mg sulfamethoxazole), the maximum tolerated dose in humans is unknown.

Signs and symptoms of overdosage reported with sulfonamides include anorexia, colic, nausea, vomiting, dizziness, headache, drowsiness and unconsciousness. Pyrexia, hematuria and crystalluria may be noted. Blood dyscrasias and jaundice are potential late manifestations of overdosage.

Signs of acute overdosage with trimethoprim include nausea, vomiting, dizziness, headache, mental depression, confusion and bone marrow depression.

General principles of treatment include the administration of intravenous fluids if urine output is low and renal function is normal. Acidification of the urine will increase renal elimination of trimethoprim. The patient should be monitored with blood counts and appropriate blood chemistries, including electrolytes. If a significant blood dyscrasia or jaundice occurs, specific therapy should be instituted for these complications. Peritoneal dialysis is not effective and hemodialysis is only moderately effective in eliminating trimethoprim and sulfamethoxazole.

Chronic

Use of Sulfamethoxazole and trimethoprim injection at high doses and/or for extended periods of time may cause bone marrow depression manifested as thrombocytopenia, leukopenia and/or megaloblastic anemia. If signs of bone marrow depression occur, the patient should be given leucovorin 5 to 15 mg daily until normal hematopoiesis is restored.

11 DESCRIPTION

Sulfamethoxazole and trimethoprim injection, a sterile solution for intravenous infusion only, is a combination of sulfamethoxazole, a sulfonamide antimicrobial, and trimethoprim, a dihydrofolate reductase inhibitor antibacterial. Each mL contains Sulfamethoxazole, USP 80 mg; trimethoprim, USP 16 mg; benzyl alcohol 10 mg (1.0% v/v and 1.0% w/v) as preservatives; diethanolamine 3 mg (0.3% v/v and 0.3% w/v); ethyl alcohol 100 mg (12.3%v/v and 10.0% w/v); propylene glycol 400 mg (38.6% v/v and 40.0% w/v); sodium metabisulfite 1 mg as an antioxidant; water for injection q.s.; air replaced with nitrogen; pH adjusted with sodium hydroxide and/or hydrochloric acid if necessary.

Trimethoprim is 2,4-diamino-5-(3,4,5-trimethoxybenzyl)pyrimidine. It is a white to light yellow, odorless, bitter compound with a molecular weight of 290.3 and the following structural formula:

C14H18N4O3 M.W. 290.3

Sulfamethoxazole is N^1-(5-methyl-3-isoxazolyl) sulfanilamide. It is an almost white, odorless, tasteless compound with a molecular weight of 253.28 and the following structural formula:

C10H11N3O3S M.W. 253.28

12 CLINICAL PHARMACOLOGY

12.1 Mechanism of Action

Sulfamethoxazole and trimethoprim injection is an antimicrobial drug [see Microbiology (12.4)].

12.3 Pharmacokinetics

Following a 1-hour intravenous infusion of a single dose of 160 mg trimethoprim and 800 mg sulfamethoxazole to 11 patients whose weight ranged from 105 lbs to 165 lbs (mean, 143 lbs), the peak plasma concentrations of trimethoprim and sulfamethoxazole were 3.4 ± 0.3 μg/mL and 46.3 ± 2.7 μg/mL, respectively. Following repeated intravenous administration of the same dose at 8-hour intervals, the mean plasma concentrations just prior to and immediately after each infusion at steady state were 5.6 ± 0.6 μg/mL and 8.8 ± 0.9 μg/mL for trimethoprim and 70.6 ± 7.3 μg/mL and 105.6 ± 10.9 μg/mL for sulfamethoxazole. The mean plasma half-life was 11.3 ± 0.7 hours for trimethoprim and 12.8 ± 1.8 hours for sulfamethoxazole. All of these 11 patients had normal renal function, and their ages ranged from 17 to 78 years (median, 60 years).^11

Pharmacokinetic studies in children and adults suggest an age-dependent half-life of trimethoprim, as indicated in Table 5.^12

Table 5: Half-life of Trimethoprim (TMP) in Pediatric Patients and Adults

Age (years) | No. of Patients | Mean TMP Half-life (hours)
<1 | 2 | 7.67
1-10 | 9 | 5.49
10-20 | 5 | 8.19
20-63 | 6 | 12.82

Patients with severely impaired renal function exhibit an increase in the half-lives of both components, requiring dosage regimen adjustment [see Dosage and Administration (2.2)].

Distribution

Both trimethoprim and sulfamethoxazole exist in the blood as unbound, protein-bound and metabolized forms; sulfamethoxazole also exists as the conjugated form.

Approximately 44% of trimethoprim and 70% of sulfamethoxazole are bound to plasma proteins. The presence of 10 mg percent sulfamethoxazole in plasma decreases the protein binding of trimethoprim by an insignificant degree; trimethoprim does not influence the protein binding of sulfamethoxazole.

Both trimethoprim and sulfamethoxazole distribute to sputum and vaginal fluid; trimethoprim also distributes to bronchial secretions, and both pass the placental barrier and are excreted in breast milk.

Elimination

Metabolism

Sulfamethoxazole is metabolized in humans to at least 5 metabolites: the N4-acetyl-, N4-hydroxy-, 5methylhydroxy-, N4-acetyl-5-methylhydroxy- sulfamethoxazole metabolites, and an N-glucuronide conjugate. The formation of N4-hydroxy metabolite is mediated via CYP2C9.

Trimethoprim is metabolized in vitro to 11 different metabolites, of which, five are glutathione adducts and six are oxidative metabolites, including the major metabolites, 1- and 3-oxides and the 3- and 4hydroxy derivatives.

The free forms of trimethoprim and sulfamethoxazole are considered to be the therapeutically active forms. In vitro studies suggest that trimethoprim is a substrate of P-glycoprotein, OCT1 and OCT2, and that sulfamethoxazole is not a substrate of P-glycoprotein.

Excretion

Excretion of trimethoprim and sulfamethoxazole is primarily by the kidneys through both glomerular filtration and tubular secretion. Urine concentrations of both trimethoprim and sulfamethoxazole are considerably higher than are the concentrations in the blood. The percent of dose excreted in urine over a 12-hour period following the intravenous administration of the first dose of 240 mg of trimethoprim and 1200 mg of sulfamethoxazole on day 1 ranged from 17% to 42.4% as free trimethoprim; 7% to 12.7% as free sulfamethoxazole; and 36.7% to 56% as total (free plus the N4-acetylated metabolite) sulfamethoxazole. When administered together as Sulfamethoxazole and trimethoprim injection, neither trimethoprim nor sulfamethoxazole affects the urinary excretion pattern of the other.

Specific Populations

Geriatric Patients: The pharmacokinetics of sulfamethoxazole 800 mg and trimethoprim 160 mg were studied in six geriatric subjects (mean age: 78.6 years) and six young healthy subjects (mean age: 29.3 years) using a non-US approved formulation. Pharmacokinetic values for sulfamethoxazole in geriatric subjects were similar to those observed in young adult subjects. The mean renal clearance of trimethoprim was significantly lower in geriatric subjects compared with young adult subjects (19 mL/h/kg vs. 55 mL/h/kg). However, after normalizing by body weight, the apparent total body clearance of trimethoprim was on average 19% lower in geriatric subjects compared with young adult subjects.

12.4 Microbiology

Mechanism of Action

Sulfamethoxazole inhibits bacterial synthesis of dihydrofolic acid by competing with para-aminobenzoic acid (PABA). Trimethoprim blocks the production of tetrahydrofolic acid from dihydrofolic acid by binding to and reversibly inhibiting the required enzyme, dihydrofolate reductase. Thus, sulfamethoxazole and trimethoprim injection blocks two consecutive steps in the biosynthesis of nucleic acids and proteins essential to many bacteria.

Resistance

In vitro studies have shown that bacterial resistance develops more slowly with both sulfamethoxazole and trimethoprim in combination than with either trimethoprim or sulfamethoxazole alone.

Antimicrobial Activity

Sulfamethoxazole and trimethoprim injection has been shown to be active against most isolates of the following microorganisms, both in in vitro and in clinical infections [see Indications and Usage (1)].

Aerobic gram-negative bacteria

Escherichia coli

Klebsiella species

Enterobacter species

Morganella morganii

Proteus mirabilis

Proteus vulgaris

Shigella flexneri

Shigella sonnei

Other Microorganisms

Pneumocystis jirovecii

The following in vitro data are available, but their clinical significance is unknown. At least 90 percent of the following bacteria exhibit an in vitro minimum inhibitory concentration (MIC) less than or equal to the susceptible breakpoint for sulfamethoxazole and trimethoprim injection against isolates of similar genus or organism group. However, the efficacy of sulfamethoxazole and trimethoprim injection in treating clinical infections caused by these bacteria has not been established in adequate and well-controlled clinical trials.

Aerobic gram-positive bacteria

Streptococcus pneumoniae

Aerobic gram-negative bacteria

Haemophilus influenzae

Susceptibility Testing

For specific information regarding susceptibility test interpretive criteria and associated test methods and quality control standards recognized by FDA for this drug, please see: https://www.fda.gov/STIC.

13 NONCLINICAL TOXICOLOGY

13.1 Carcinogenesis, Mutagenesis, Impairment of Fertility

Carcinogenesis

Sulfamethoxazole was not carcinogenic when assessed in a 26-week tumorigenic mouse (Tg-rasH2) study at doses up to 400 mg/kg/day sulfamethoxazole; equivalent to 2-fold the human systemic exposure (at a daily dose of 800 mg sulfamethoxazole twice a day).

Mutagenesis

In vitro reverse mutation bacterial tests according to the standard protocol have not been performed with sulfamethoxazole and trimethoprim in combination. An in vitro chromosomal aberration test in human lymphocytes with sulfamethoxazole/trimethoprim was negative. In in vitro and in vivo tests in animal species, sulfamethoxazole/trimethoprim did not damage chromosomes. In vivo micronucleus assays were positive following oral administration of sulfamethoxazole/trimethoprim. Observations of leukocytes obtained from patients treated with sulfamethoxazole and trimethoprim revealed no chromosomal abnormalities.

Sulfamethoxazole alone was positive in an in vitro reverse mutation bacterial assay and in in vitro micronucleus assays using cultured human lymphocytes.

Trimethoprim alone was negative in in vitro reverse mutation bacterial assays and in in vitro chromosomal aberration assays with Chinese Hamster ovary or lung cells with or without S9 activation. In in vitro Comet, micronucleus and chromosomal damage assays using cultured human lymphocytes, trimethoprim was positive. In mice following oral administration of trimethoprim, no DNA damage in Comet assays of liver, kidney, lung, spleen, or bone marrow was recorded.

Impairment of Fertility

No adverse effects on fertility or general reproductive performance were observed in rats given oral dosages as high as 350 mg/kg/day sulfamethoxazole plus 70 mg/kg/day trimethoprim, doses roughly two times the recommended human daily dose on a body surface area basis.

15 REFERENCES

1. Winston DJ, Lau WK, Gale RP, Young LS. Trimethoprim-Sulfamethoxazole for the Treatment of Pneumocystis carinii pneumonia. Ann Intern Med. June 1980;92:762-769.

2. Al-Khatib SM, LaPointe N, Kramer JM, Califf RM. What Clinicians Should Know About the QT Interval. JAMA. 2003;289(16):2120-2127.

3. Boyer EW, Stork C, Wang RY. Review: The Pharmacology and Toxicology of Dofetilide. Int J Med Toxicol. 2001;4(2):16.

4. Safrin S, Lee BL, Sande MA. Adjunctive folinic acid with trimethoprim-sulfamethoxazole for Pneumocystis carinii pneumonia in AIDS patients is associated with an increased risk of therapeutic failure and death. J Infect Dis. Oct 1994;170(4):912-7.

5. London NJ, Garg SJ, Moorthy RS, Cunningham ET. Drug-induced uveitis. J Ophthalmic Inflamm Infect. 2013;3:43.

6. Marinella MA. Trimethoprim-induced hyperkalemia: An analysis of reported cases. Gerontol. 1999;45:209–212.

7. Margassery S, Bastani B. Life threatening hyperkalemia and acidosis secondary to trimethoprimsulfamethoxazole treatment. J. Nephrol. 2001;14(5):410-414.

8. Moh R, et al. Haematological changes in adults receiving a zidovudine-containing HAART regimen in combination with cotrimoxazole in Côte d'Ivoire. Antivir Ther. 2005;10(5):615-24.

9. Kosoglou T, Rocci ML Jr, Vlasses PH. Trimethoprim alters the disposition of procainamide and Nacetylprocainamide. Clin Pharmacol Ther. Oct 1988;44(4):467-77.

10. Brumfitt W, Pursell R. Trimethoprim/Sulfamethoxazole in the Treatment of Bacteriuria in Women. J Infect Dis. Nov 1973;128 (Suppl): S657-S663.

11. Grose WE, Bodey GP, Loo TL. Clinical Pharmacology of Intravenously Administered Trimethoprim-Sulfamethoxazole. Antimicrob Agents Chemother. Mar 1979;15:447-451.

12. Siber GR, Gorham C, Durbin W, Lesko L, Levin MJ. Pharmacology of Intravenous Trimethoprim-Sulfamethoxazole in Children and Adults. Current Chemotherapy and Infectious Diseases. American Society for Microbiology, Washington, D.C. 1980; Vol. 1, pp. 691-692.

16 HOW SUPPLIED/STORAGE AND HANDLING

Sulfamethoxazole and trimethoprim injection, USP is supplied as follows:

5 mL Single Dose Vial containing 80 mg trimethoprim (16 mg/mL) and 400 mg sulfamethoxazole (80 mg/mL) for infusion with 5% dextrose in water.

5 mL Vial: NDC 70069-361-01

5 mL Vial (Box of 10): NDC 70069-361-10

10 mL Multiple Dose Vial; Each 5 mL containing 80 mg trimethoprim (16 mg/mL) and 400 mg sulfamethoxazole (80 mg/mL) for infusion with 5% dextrose in water.

10 mL Vial: NDC 70069-362-01

10 mL Vial (Box of 10): NDC 70069-362-10

30 mL Multiple Dose Vial; Each 5 mL containing 80 mg trimethoprim (16 mg/mL) and 400 mg sulfamethoxazole (80 mg/mL) for infusion with 5% dextrose in water.

30 mL Vial (Box of 1): NDC 70069-363-01

Store at 20° to 25°C (68° to 77°F) [see USP Controlled Room Temperature]. DO NOT REFRIGERATE.

17 PATIENT COUNSELING INFORMATION

Embryo–fetal Toxicity

Advise female patients of reproductive potential that sulfamethoxazole and trimethoprim injection can cause fetal harm and to inform their healthcare provider of a known or suspected pregnancy [see Use in Specific Populations (8.1)].

Hypersensitivity and Other Serious or Fatal Reactions

Advise patients to stop taking sulfamethoxazole and trimethoprim injection immediately if they experience any clinical signs such as rash, pharyngitis, fever, arthralgia, cough, chest pain, dyspnea, pallor, purpura or jaundice and to contact their healthcare provider as soon as possible [see Warnings and Precautions (5.2) and Adverse Reactions (6.1)].

Lactation

Advise nursing women to avoid breastfeeding during treatment with sulfamethoxazole and trimethoprim injection.

Antibacterial Resistance

Counsel patients that antibacterial drugs including sulfamethoxazole and trimethoprim injection should only be used to treat bacterial infections. It does not treat viral infections (e.g., the common cold).

Instruct patients to maintain an adequate fluid intake in order to prevent crystalluria and stone formation.

Diarrhea

Advise patients that diarrhea is a common problem caused by antibiotics which usually ends when the antibiotic is discontinued. Sometimes after starting treatment with antibiotics, patients can develop watery and bloody stools (with or without stomach cramps and fever) even as late as two or more months after having taken the last dose of the antibiotic. If this occurs, patients should contact their physician as soon as possible.

Trademarks are the property of their respective owners.

Manufactured for:

Somerset Therapeutics, LLC

Somerset, NJ 08873

Made in India

Code No.: KR/DRUGS/KTK/28/289/97

ST-STM/P/03

1201168

PACKAGE LABEL.PRINCIPAL DISPLAY PANEL

5 mL Container Label

5 mL Container Label

Carton Label (10 X 5 mL Single-Dose Vials)

Carton Label

10 mL Container Label

10 mL Container Label

Carton Label (10 X 10 mL Multiple-Dose Vials)

Carton Label (10 X 10 mL Single-Dose Vials)

30 mL Container Label

30 mL Container Label

Carton Label (30 mL Multiple-Dose Vial)

Carton Label (30 mL Multiple-Dose Vial)